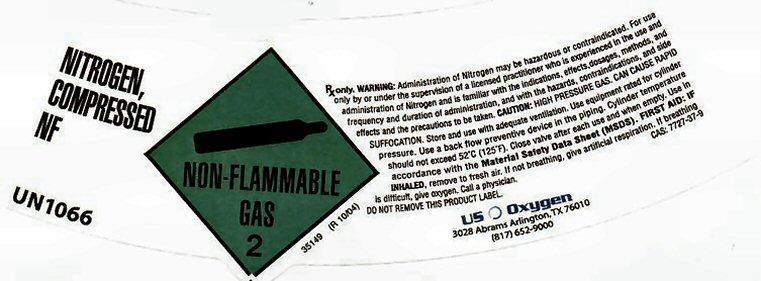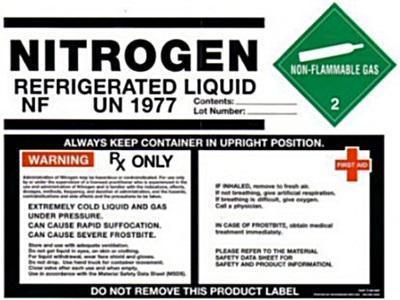 DRUG LABEL: NITROGEN
NDC: 54632-002 | Form: GAS
Manufacturer: U.S. Oxygen and Supply, LLC
Category: prescription | Type: HUMAN PRESCRIPTION DRUG LABEL
Date: 20140221

ACTIVE INGREDIENTS: NITROGEN 99 L/100 L

NITROGEN REFRIGERATED LIQ NF

NITROGEN
REFRIGERATED LIQUID
NF UN1977 NON-FLAMMABLE GAS 2 41977

Contents:________________
Lot Number:______________

ALWAYS KEEP CONTAINER IN UPRIGHT POSITION.
Rx ONLY
WARNING: Administration of Nitrogen may be hazardous or contraindicated. For use only by or under the supervision
of a licensed practitioner who is experienced in the use and administration of Nitrogen and is familiar with the
indications, effects, dosages, methods, and frequency and duration of administration,and the hazards,
contraindications, and side effects and the precautions to be taken.
EXTREMELY COLD LIQUID AND GAS UNDER PRESSURE.
CAN CAUSE RAPID SUFFOCATION.
CAN CAUSE SEVERE FROSTBITE.

Store and use with adequate ventilation.
Do not get liquid in eyes, on skin or clothing.
For liquid withdraw, wear face shield and gloves.
Do not drop. Use suitable hand truck for container movement.
Close valve after each use and when empty.
Use in accordance with the Material Safety Data Sheet (MSDS).

FIRST AID:
IF INHALED, remove to fresh air.
If not breathing, give artificial respiration.
If breathing is difficult, give oxygen.
Call a physician.

IN CASE OF FROSTBITE, obtain medical treatment immediately.

PLEASE REFER TO THE MATERIAL SAFETY DATA SHEET FOR SAFETY AND PRODUCT INFORMATION.
DO NOT REMOVE THIS PRODUCT LABEL.

NITROGEN COMPRESSED NF UN1066

NON-FLAMMABLE GAS 2

Rx only. WARNING: Administration of Nitrogen may be hazardous or contraindicated. For the use only by or under the supervision of a licensed practitioner who is experienced in the use and administration of Nitrogen and is familiar with the indications, effects, dosages, methods, and frequency and duration of administration., and with the hazards, contraindications, and side effects and the precautions to be taken. CAUTION: HIGH PRESSURE GAS. CAN CAUSE RAPID SUFFOCATION. Store and use with adequate ventilation. Use equipment rated for cylinder pressure. Use a back flow preventive device in the piping. Cylinder temperature should not exceed 52° C (125° F). Close valve after each use and when empty. Use in accordance with the Material Safety Data Sheet (MSDS). FIRST AID: IF INHALED, remove to fresh air. If not breathing, give artificial respiration. If breathing is difficult, give oxygen. Call a physician.

DO NOT REMOVE THIS PRODUCT LABEL CAS: 7727-37-9

US Oxygen
3028 Abrams Arlington, TX 76010
(817) 652-9000